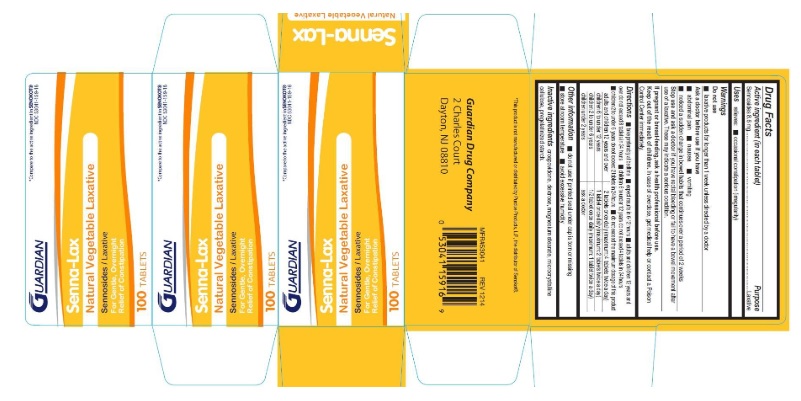 DRUG LABEL: Senna-Lax
NDC: 53041-159 | Form: TABLET
Manufacturer: Guardian Drug Company
Category: otc | Type: HUMAN OTC DRUG LABEL
Date: 20241219

ACTIVE INGREDIENTS: SENNOSIDES 8.6 mg/1 1
INACTIVE INGREDIENTS: CROSPOVIDONE; DEXTROSE; MAGNESIUM STEARATE; MICROCRYSTALLINE CELLULOSE; STARCH, PREGELATINIZED CORN

Senna-Lax

Active ingredient (in each tablet)

Sennosides 8.6 mg

Purpose

Laxative

Uses

relieves: occasional constipation (irregularity)

WARNINGS

Do not use

- laxative products for longer than 1 week unless directed by a doctor

Ask a doctor before use if you have

- abdominal pain
- nausea
- vomiting
- noticed a sudden change in bowel habits that continues over a period of 2 weeks

stop use and ask a doctor if

you have rectal bleeding or fail to have a bowel movement after use of a laxative. These may indicate a serious condition.

If pregnant or breast-feeding, ask a health professional before use

keep out of reach of children. In case of overdose, get medical help or contact a poison control center immediately.

Directions

- take preferably at bedtime
- expect results in 6-12 hours
- adults and children 12 years and over do not exceed 8 tablets in 24 hours
- children 6 to under 12 years do not exceed 4 tablets in 24 hours
- children 2 to under 6 years do not exceed 2 tablets in 24 hours
- do not exceed the maximum dosage of this product

adults and children 12 years and over | 2 tablets once daily (maximum: 4 tablets twice a day)
children 6 to under 12 years | 1 tablet once daily (maximum: 2 tablets twice a day)
children 2 to under 6 years | 1/2 tablet once daily (maximum: 1 tablet twice a day)
childrem under 2 years | ask a doctor

Other information

- do not use if printed seal under cap is torn or missing
- store at room temperature
- avoid excessive humidity

Inactive ingredients

crospovidone, dextrose, magnesium stearate, microcrystalline cellulose, pregelatinized starch

PDP

Compare to the active ingredient in SENOKOT®

Senna-Lax

Natural Vegetable Laxative

Sennosides / Laxative

For Gentle, Overnight

Relief of Constipation

100 Tablets